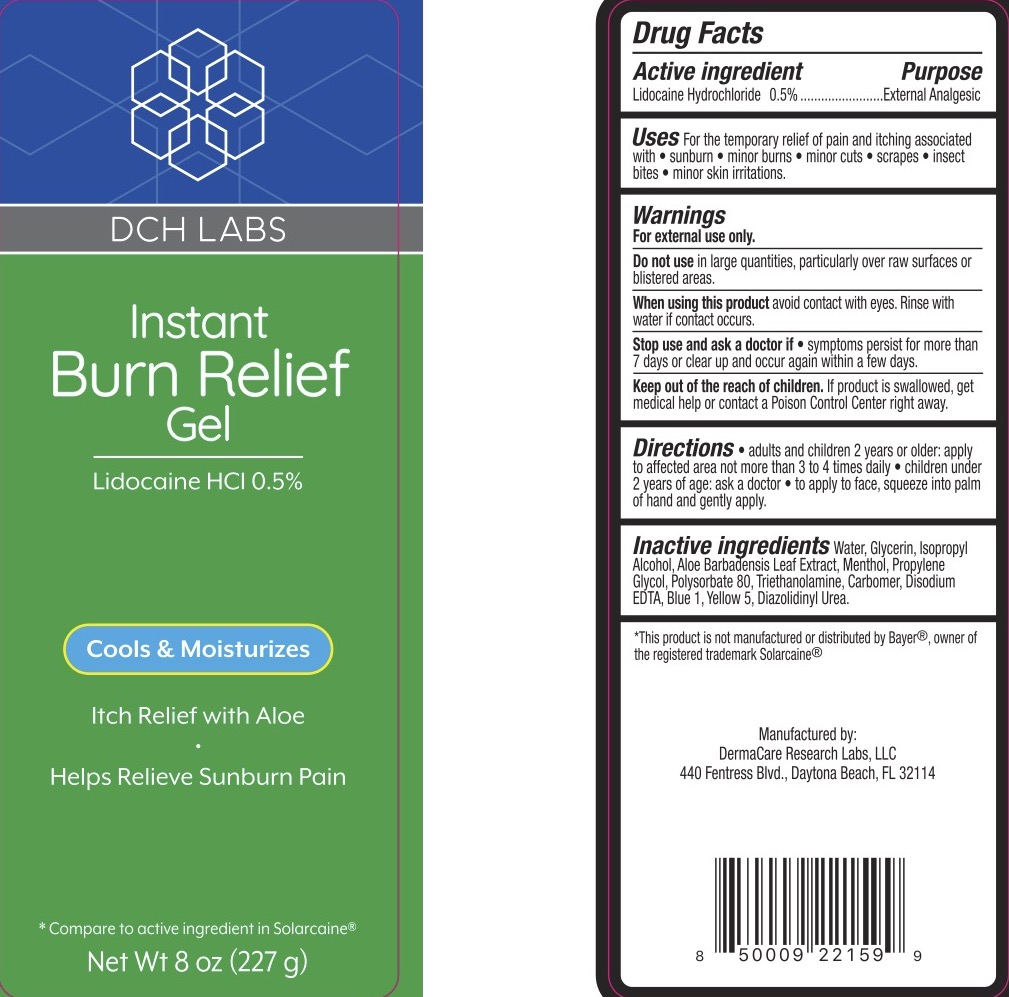 DRUG LABEL: DCH Burn Relief
NDC: 72839-955 | Form: GEL
Manufacturer: Derma Care Research Labs, LLC
Category: otc | Type: HUMAN OTC DRUG LABEL
Date: 20241220

ACTIVE INGREDIENTS: LIDOCAINE HYDROCHLORIDE 0.5 g/100 g
INACTIVE INGREDIENTS: WATER; GLYCERIN; ISOPROPYL ALCOHOL; MENTHOL; PROPYLENE GLYCOL; EDETATE DISODIUM; TROLAMINE; ALOE VERA LEAF; CARBOMER 940; POLYSORBATE 80; DIAZOLIDINYL UREA; FD&C BLUE NO. 1; FD&C YELLOW NO. 5

DCH Burn Relief Gel, Lidocaine HCl 0.5%

ACTIVE INGREDIENT

Lidocaine HCl 0.5%

PURPOSE

External Analgesic.

DOSAGE AND ADMINISTRATION

For the temporary relief of pain and itching due to sunburn, minor burns, insect bites, minor cuts, scrapes, and minor skin irritations.

WARNINGS

For external use only.

Do not use in large quantities, particularly over raw surfaces or blistered areas.

When using this product avoid contact with eyes. Rinse with water if contact occurs.

Stop use and ask a doctor if the condition worsens or symptoms persist for more than 7 days or clear up and occur again within a few days.

Keep out of reach of children. If the product is swallowed, get medical help or contact a Poison Control Center right away.

INDICATIONS AND USAGE

Adults and children 2 years and older: apply to the affected area, not more than 3 to 4 times a day. Children under 2 years of age: consult a physician. To apply to face, squeeze into palm of hand and gently apply.

INACTIVE INGREDIENT

Water, Glycerin, Isopropyl Alcohol, Aloe Barbadensis Leaf Extract, Menthol, Propylene Glycol, Polysorbate 80, Triethanolamine, Carbomer, Disodium EDTA, Blue 1, Yellow 5, Diazolidinyl Urea.